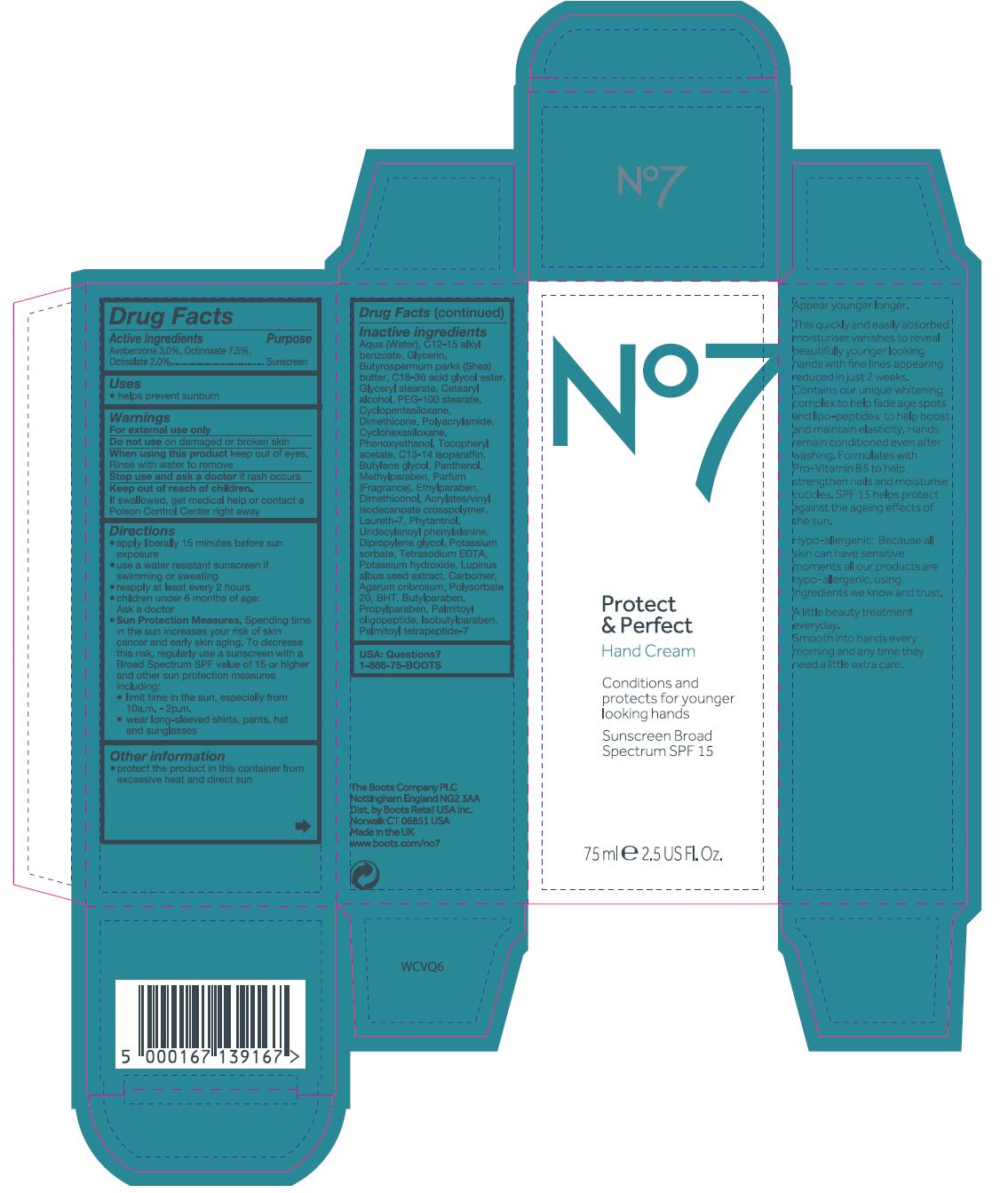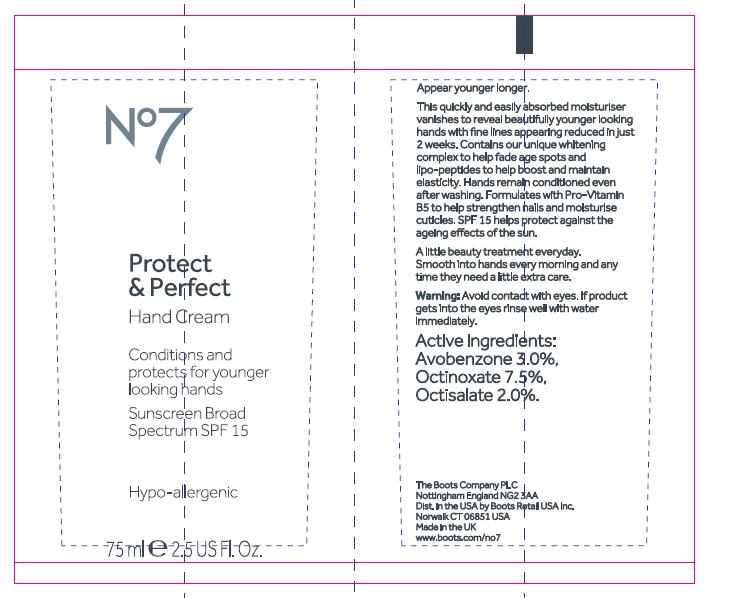 DRUG LABEL: No7 Protect and Perfect Hand Cream Sunscreen Broad Spectrum SPF 15
NDC: 11489-076 | Form: CREAM
Manufacturer: BCM Ltd
Category: otc | Type: HUMAN OTC DRUG LABEL
Date: 20120501

ACTIVE INGREDIENTS: Avobenzone 2.25 mL/75 mL; Octinoxate 5.625 mL/75 mL; Octisalate 1.5 mL/75 mL
INACTIVE INGREDIENTS: Water; ALKYL (C12-15) BENZOATE; Glycerin; SHEA BUTTER; GLYCERYL MONOSTEARATE; CETOSTEARYL ALCOHOL; PEG-100 STEARATE; CYCLOMETHICONE 5; Dimethicone; CYCLOMETHICONE 6; Phenoxyethanol; .ALPHA.-TOCOPHEROL ACETATE; C13-14 ISOPARAFFIN; BUTYLENE GLYCOL; PANTHENOL; METHYLPARABEN; ETHYLPARABEN; LAURETH-7; PHYTANTRIOL; DIPROPYLENE GLYCOL; POTASSIUM SORBATE; EDETATE SODIUM; potassium hydroxide; LUPINUS ALBUS SEED; AGARUM CLATHRATUM; POLYSORBATE 20; BUTYLATED HYDROXYTOLUENE; BUTYLPARABEN; PROPYLPARABEN; PALMITOYL OLIGOPEPTIDE; ISOBUTYLPARABEN; PALMITOYL TETRAPEPTIDE-7

Carton and tube labelling

ACTIVE INGREDIENT

Active Ingredients Avobenzone 3.0%, Octinoxate 7.5%, Octisalate 2.0%

Purpose Sunscreen

PURPOSE

Uses helps prevent sunburn

Warnings

For external use only

Do not use on damaged or broken skin

When using this product keep out if eyes. Rinse with water to remove.

Stop use and ask a doctor if rash occurs.

Keep out of reach of children. If swallowed get medical help or contact a poison control center right away.

INDICATIONS AND USAGE

Directons

Apply liberally 15 minutes before sun exposure

Use a water resistant sunscreen if swimming or sweating

Reapply at least every 2 hours

Chidren under 6 months of age: Ask a doctor

Sun Protection Measures

Spending time in the sun increases your risk of skin cancer and early skin aging. To decrease this risk, regularly use a sunscreen with a broad spectrum SPF value of 15 or higher and other sun protection measures including:

limit time in the sun, especially from 10a,m - 2p.m

wear long-sleeved shirts, pants, hat and sunglasses

Other information

Protect the product in this container from excessive heat and direct sun

Inactive Ingredients

Aqua (water), C12-15 alkyl benzoate, Glycerin, Butyrospermum parkii (shea) butter,C18-36 acid glycol ester, Glyceryl stearate, Cetearyl alcohol, PEG-100 stearate, Cyclopentasiloxane, Dimethicone, Polyacrylamide, Cyclohexasiloxane, Phenoxyethanol, Tocopheryl acetate, C13-14 isoparaffin, Butylene glycol, Panthenol, Methylparaben, Parfum (Fragrance), Ethylparaben, Dimethiconol, Acrylates/vinyl isodecanoate crosspolymer, Laureth-7, Phytantiol, Undecylenyl phenylalanine, Dipropylene glycol, Potassium sorbate, Tetrasodium EDTA, Potassium hydroxide, Lupinus albus seed extract, Carbomer, Agarum cribosum, Polysorbate 20, BHT, Butylparaben, Propylparaben, Palmitoyl oligopeptide, Isobutylparaben, Palmitoyl tetrapeptide-7

USA: Questions? 1-866-75-BOOTS

DESCRIPTION

Appear younger longer.
This quickly and easily absorbed moisturiser vanishes to reveal beautifully younger looking hands with fine lines reduced in just 2 weeks.
Contains our unique whitening complex to help fade age spots and lipo-peptides to help boost and maintain elasticity. Hands remain conditioned even after washing. Formulates with pro-vitamin B5 to help strengthen nails and moisturise cuticles. SPF 15 helps protect against the ageing effects of the sun.
Hypo-allergenic: Because all skin can have sensitive moments all our products are hypo-allergenic using ingredients we known and trust.
A little beauty treatment everyday.

PATIENT COUNSELING INFORMATION

The Boots company PLC Nottingham England NG2 3AA
Dist. by Boots Retail USA Inc. Norwalk CT 06851 USA
Made in the UK
www.Boots.com/no7

INSTRUCTIONS FOR USE

Smooth into hands every morning and any time they need a little extra care.

ACTIVE INGREDIENT

TUBE TEXT

Active ingredients: Avobenzone 3.0%, Octinoxate 7.5%, Octisalate 2.0%

WARNINGS

TUBE TEXT

Warning: Avoid contact with eyes. If product gets into the eyes rinse well with water immediately.

INDICATIONS AND USAGE

TUBE TEXT

Smooth into hands every morning and any time they need a little extra care.

PATIENT COUNSELING INFORMATION

TUBE TEXT

The Boots Company PLC Nottingham England NG2 3AA
Dist. in the USA by Boots Retail USA Inc. Norwalk CT 06851 USA
Made in the UK
www.Boots.com/no7

DESCRIPTION

TUBE TEXT
Appear younger longer.
This quickly and easily absorbed moisturiser vanishes to reveal beautifully younger looking hands with fine lines appearing reduced in just 2 weeks. Contains our unique whitening complex to help fade age spots and lipo-peptides to help boost and maintain elasticity. Hands remain conditioned even after washing. Formulates with Pro-Vitamin B5 to help strengthen nails and moisturise cuticles. SPF 15 helps protect against the ageing effects of the sun.
A little beauty treatment everyday.

PACKAGE LABEL

No7 Protect and Perfect
Hand Cream
Conditions and protects for younger looking hands
Sunscreen Broad Spectrum SPF 15
75ml 2.5 US Fl.Oz.
No7 PP Hand Cream SPF 15 carton.jpg

PACKAGE LABEL

No7 Protect and Perfect

Hand Cream

Conditions and protects for younger looking hands

Sunscreen Broad Spectrum SPF 15

Hypo-allergenic

75ml 2.5 US Fl.Oz.

No7 PP Hand Cream SPF 15 tube.jpg